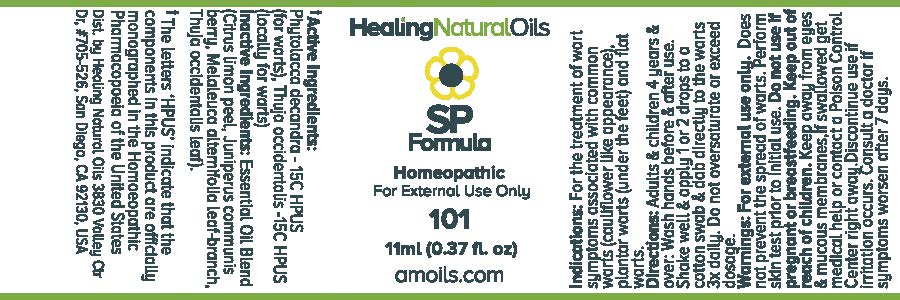 DRUG LABEL: SP1 Formula
                
NDC: 61077-101 | Form: OIL
Manufacturer: Healing Natural Oils LLC
Category: homeopathic | Type: HUMAN OTC DRUG LABEL
Date: 20171227

ACTIVE INGREDIENTS: PHYTOLACCA AMERICANA ROOT 15 [hp_C]/11 mL; THUJA OCCIDENTALIS LEAFY TWIG 15 [hp_C]/11 mL
INACTIVE INGREDIENTS: LEMON PEEL; JUNIPER BERRY; MELALEUCA ALTERNIFOLIA LEAF; THUJA OCCIDENTALIS LEAF

Active Ingredients:

Phytolacca decandra - 15C HPUS
Thuja occidentalis - 15C HPUS

Purpose

Phytolacca decandra - 15C HPUS (for warts),
Thuja occidentalis -15C HPUS (locally for warts)
The letters ‘HPUS’ indicate that the components in this product are officially
monographed in the Homoeopathic Pharmacopoeia of the United States

Inactive Ingredients:

Essential Oil Blend (Citrus limon peel,
Juniperus communis berry, Melaleuca alternifolia leaf-branch, Thuja occidentalis leaf)

Indications:

For the treatment of wart symptoms associated with common warts (cauliflower like appearance), plantar warts (under the feet) and flat warts.

Directions:

Adults and children 4 years and over: Wash hands before and after use.
Shake well and apply 1 or 2 drops to a cotton swab and dab directly to warts 3x daily.
Do not oversaturate or exceed dosage.

Warnings:

For external use only.

Does not prevent the spread of warts.

Perform skin test prior to initial use.

Do not use if pregnant or breastfeeding.

Keep out of reach of children.

OTHER SAFETY INFORMATION

Keep away from eyes and mucous membranes. If swallowed get medical help
or contact a Poison Control Center right away.

Discontinue use if irritation occurs.

ASK DOCTOR

Consult a doctor if symptoms worsen after 7 days.

DESCRIPTION

Dist. by Healing Natural Oils 3830 Valley Ctr Dr, #705-526, San Diego, CA 92130, USA

PACKAGE LABEL

Healing Natural Oils

SP1
Formula

Homeopathic

For External Use Only

101

11ml (0.37 fl. oz)
amoils.com